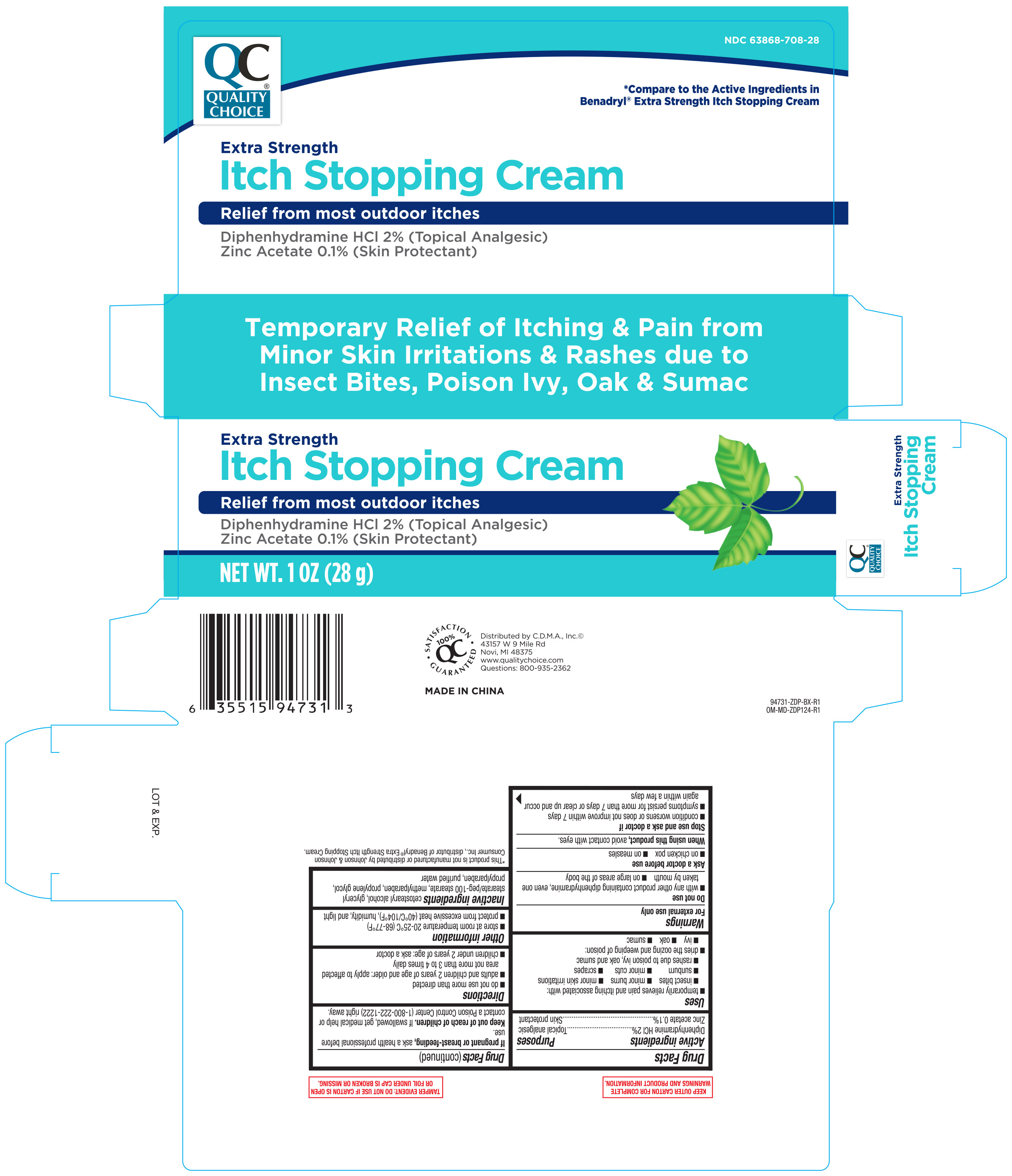 DRUG LABEL: Anti itch Topical Analgesic
NDC: 63868-708 | Form: CREAM
Manufacturer: Chain Drug Marketing Associations Inc
Category: otc | Type: HUMAN OTC DRUG LABEL
Date: 20200727

ACTIVE INGREDIENTS: DIPHENHYDRAMINE HYDROCHLORIDE 2 g/100 g; ZINC ACETATE 0.1 g/100 g
INACTIVE INGREDIENTS: WATER; PROPYLPARABEN; CETOSTEARYL ALCOHOL; GLYCERYL STEARATE/PEG-100 STEARATE; METHYLPARABEN; PROPYLENE GLYCOL

Quality Choice Extra Strength Itch Stopping Cream 1 oz. 94731 ZDP 2020

Active Ingredients Purpose

Diphenhydramine HCI 2%........................................................Topical analgesic

Zinc acetate, 0.1%.................................................................... Skin protectant

Uses

- temporarily relieves pain and itching associated with:
- insect bites
- minor burns
- minor skin irritations
- sunburn
- minor cuts
- scrapes
- rashes due to poison ivy, oak, and sumac
- dries the oozing and weeping of poison:
- ivy
- oak
- sumac

Warnings

For external use only

Do not use

- with any other product containing diphenhydramine, even one taken by mouth
- on large areas of the body

Ask a doctor before use

- on chicken pox
- on measles

When using this product avoid contact with the eyes

Stop use and ask a doctor if

- condition worsens or does not improve within 7 days
- symptoms persist for more than 7 days or clear up and occur again within a few days

PREGNANCY OR BREAST FEEDING

If pregnant or breast-feeding, ask a health professional before use.

Keep out of reach of children

If swallowed, get medical help or contact a Poison Control Center right away

Directions

- do not use more than directed
- adults and children 2 years of age and older: apply to affected area not more than 3 to 4 times daily
- children under 2 years of age: ask a doctor

Other information

- store at room temperature 20-25°C (68-77°F)
- protect from excessive heat (40°C/104°F), humidity, and light

inactive ingredients

cetostearyl alcohol, glyceryl stearate/peg-100 stearate, methylparaben, propylene glycol, propylparaben, purified water

DOSAGE AND ADMINISTRATION

DISTRIBUTED BY:

C.D.M.A. INC.

43157 W. 9 Mile Road

Novi, MI 48375

www.qualitychoice.com

Made in China